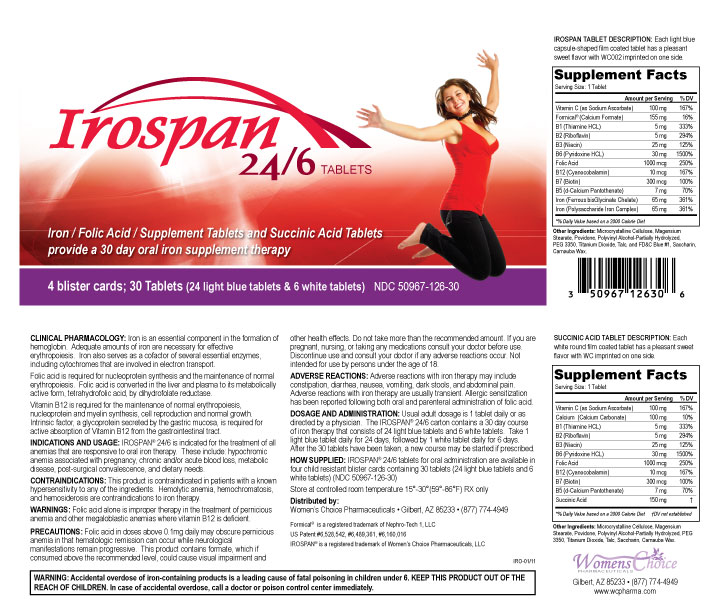 DRUG LABEL: IROSPAN 24/6
NDC: 50967-126 | Form: KIT | Route: ORAL
Manufacturer: WOMENS CHOICE PHARMACEUTICALS LLC
Category: prescription | Type: HUMAN PRESCRIPTION DRUG LABEL
Date: 20250513

ACTIVE INGREDIENTS: SODIUM ASCORBATE 100 mg/1 1; CALCIUM FORMATE 155 mg/1 1; THIAMINE HYDROCHLORIDE 5 mg/1 1; RIBOFLAVIN SODIUM 5 mg/1 1; NIACIN 25 mg/1 1; PYRIDOXINE HYDROCHLORIDE 30 mg/1 1; FOLIC ACID 1 mg/1 1; CYANOCOBALAMIN 10 ug/1 1; IRON DEXTRAN 65 mg/1 1; BIOTIN 300 ug/1 1; CALCIUM PANTOTHENATE 300 ug/1 1; FERROUS BISGLYCINATE 65 mg/1 1; SODIUM ASCORBATE 100 mg/1 1; CALCIUM CARBONATE 100 mg/1 1; THIAMINE HYDROCHLORIDE 5 mg/1 1; RIBOFLAVIN 5 mg/1 1; NIACIN 25 mg/1 1; PYRIDOXINE HYDROCHLORIDE 30 mg/1 1; FOLIC ACID 1 mg/1 1; CYANOCOBALAMIN 10 ug/1 1; BIOTIN 300 ug/1 1; CALCIUM PANTOTHENATE 7 mg/1 1; SUCCINIC ACID 150 mg/1 1
INACTIVE INGREDIENTS: CELLULOSE, MICROCRYSTALLINE; MAGNESIUM STEARATE; POVIDONE; POLYVINYL ALCOHOL; POLYETHYLENE GLYCOL 3350; TITANIUM DIOXIDE; TALC; FD&C BLUE NO. 1; SACCHARIN; CARNAUBA WAX; CELLULOSE, MICROCRYSTALLINE; MAGNESIUM STEARATE; POVIDONE; POLYVINYL ALCOHOL; POLYETHYLENE GLYCOL 3350; TITANIUM DIOXIDE; TALC; SACCHARIN; CARNAUBA WAX

Irospan 24/6

DESCRIPTION

IROSPAN TABLET DESCRIPTION : Each light blue capsule-shaped film coated tablet has a pleasant sweet flavor with WC002 imprinted on one side.

SUCCINIC ACID TABLET DESCRIPTION: Each white round film coated tablet has a pleasant sweet flavor with WC imprinted on one side.

CLINICAL PHARMACOLOGY

Clinical Pharmacology : Iron is an essential component in the formation of hemoglobin. Adequate amounts of iron are necessary for effective erthropoiesis. Iron also serves as a cofactor of several essential enzymes, including cytochromes that are involved in electron transport.

Folic acid is required for nucleoprotein synthesis and the maintenance of normal erthropoiesis. Folic acid is converted in the liver and plasma to its metabolically active form, tetrahydrofolic acid, by dihydrofolate reductase.

Vitamin B12 is required for the maintenance of normal erthropoiesis, nucleprotein and myelin synthesis, cell reproduction and normal growth. Intrinsic factor, a glycoprotein secreted by the gastric mucosa, is required for active absorption of Vitamin B12 from the gastrointestinal tract.

INDICATIONS AND USAGE

INDICATION AND USAGE: IROSPAN 24/6 is indicated for the treatment of all anemias that are responsive to oral iron therapy. These include: hypochromic anemia associated with pregnancy, chronic and/or acute blood loss, metabolic disease, post-surgical convalescence, and dietary needs.

CONTRAINDICATIONS

Warnings: Ingestion of more than 3 grams of omega-fatty acids per day has been shown to have potential antithrombotic effects, including increased bleeding time and INR. Administration of omega-3 fatty acids should be avoided in patients on anticoagulants and in those known to have an inherited or acquired bleeding diathesis.

Folic acid alone is improper therapy in the treatment of pernicious anemia and other megaloblastic anemias where vitamin B12 is deficient.

BOXED WARNING

WARNING: Accidental overdose of iron-containing products is a leading cause of fatal poisoning in children under 6. KEEP THIS PRODUCT OUT OF THE REACH OF CHILDREN. In case of accidental overdose, call a doctor or poison control center immediately.

PRECAUTIONS

P recautions: Folic acid in doses above 0.1mg daily may obscure pernicious anemia in that hematologic remission can occur while neurological manifestations remain progressive. This product contains formate, which if consumed above the recommended level, could cause visual impairment and other health effects. Do not take more than the recommended amount. If you are pregnant, nursing, or taking any medications consult your doctor before use. Discontinue use and consult your doctor if any adverse reactions occur. Not intended for use by persons under the age of 18.

ADVERSE REACTIONS

A dverse Reactions: Allergic sensitization has been reported following both oral and parenteral administration of folic acid.

Dosage and Administration

Usual adult dosage is 1 tablet daily or as directed by a physician. The IROSPAN® carton contains a 30 day course of iron therapy that consists of 24 light blue tablets and 6 white tablets. Take 1 light blue tablet daily for 24 days, followed by 1 white tablet daily for 6 days. After the 30 tablets have been taken, a new course may be started if prescribed.

How Supplied

IROSPAN® 24/6 tablets for oral administration are available in four child resistant blister cards containing 30 tablets (24 light blue tablets and 6 white tablets) (NDC 50967-126-30)